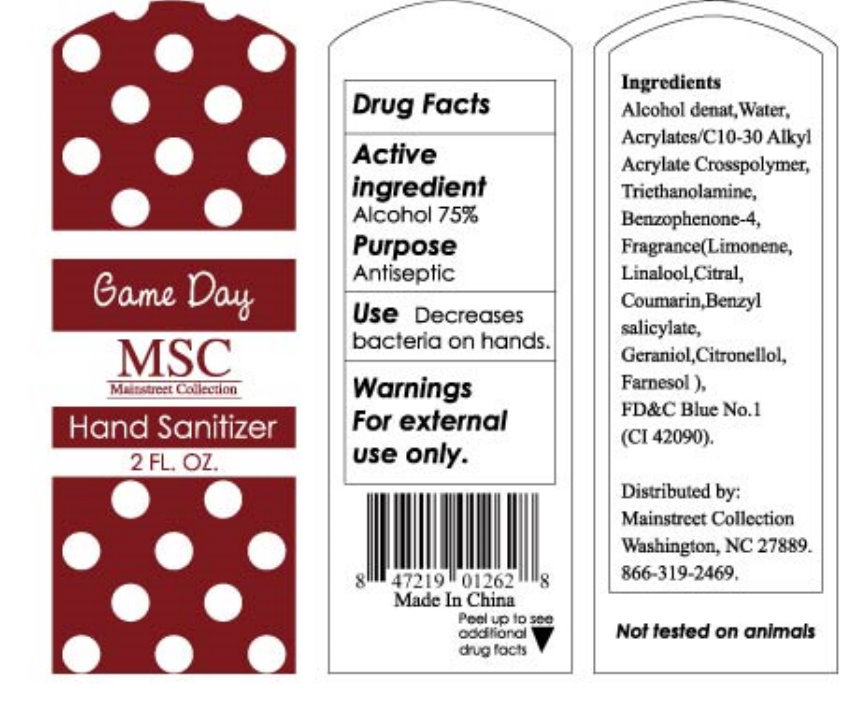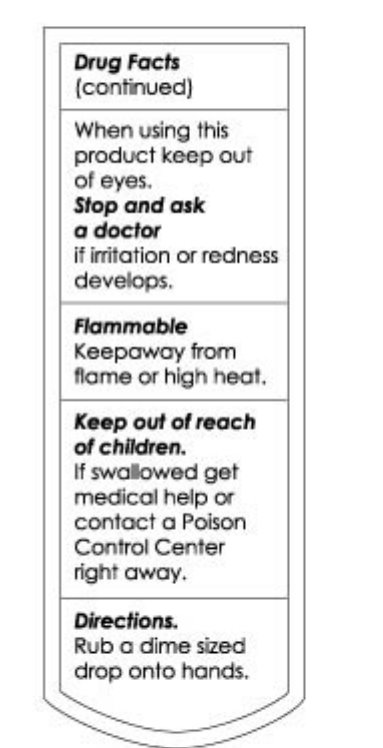 DRUG LABEL: Game Day MSC Mainstreet Collection Hand Sanitizer
NDC: 76379-100 | Form: LIQUID
Manufacturer: Mainstreet Collection
Category: otc | Type: HUMAN OTC DRUG LABEL
Date: 20110819

ACTIVE INGREDIENTS: ALCOHOL 75 mL/100 mL
INACTIVE INGREDIENTS: WATER; CARBOMER COPOLYMER TYPE A; TROLAMINE; SULISOBENZONE; LIMONENE, (+/-)-; LINALOOL, (+/-)- ; CITRAL; COUMARIN; BENZYL SALICYLATE; GERANIOL; .BETA.-CITRONELLOL, (R)-; FARNESOL; FD&C BLUE NO. 1

Game Day MSC Mainstreet Collection Hand Sanitizer

Drug Facts

Active ingredient

Alcohol 75%

Purpose

Antiseptic

INDICATIONS AND USAGE

Use Decreases bacteria on hands.

Warnings

For external use only.

When using this product keep out of eyes.

ASK DOCTOR

Stop and ask a doctor if irritation or redness develops.

STORAGE AND HANDLING

Flammable

Keep away from flame or high heat.

Keep out of reach of children.

If swallowed get medical help or contact a Poison Control Center right away.

Directions.

Rub a dime sized drop onto hands.

INACTIVE INGREDIENT

Ingredients

Alcohol denat, Water, Acrylates/C10-30 Alkyl Acrylate Crosspolymer, Triethanolamine, Benzophenone-4, Fragance(Limonene, Linalool, Citral, Coumarin, Benzyl salicylate, Geraniol, Citronellol, Farnesol), FD C Blue No.1 (CI 42090).

Distributed by:

Mainstreet Collection

Washington, NC 27889.

Not tested on animals

Made In China

PACKAGE LABEL

Game Day

MSC

Mainstreet Collection

Hand Sanitizer

2 FL. OZ.